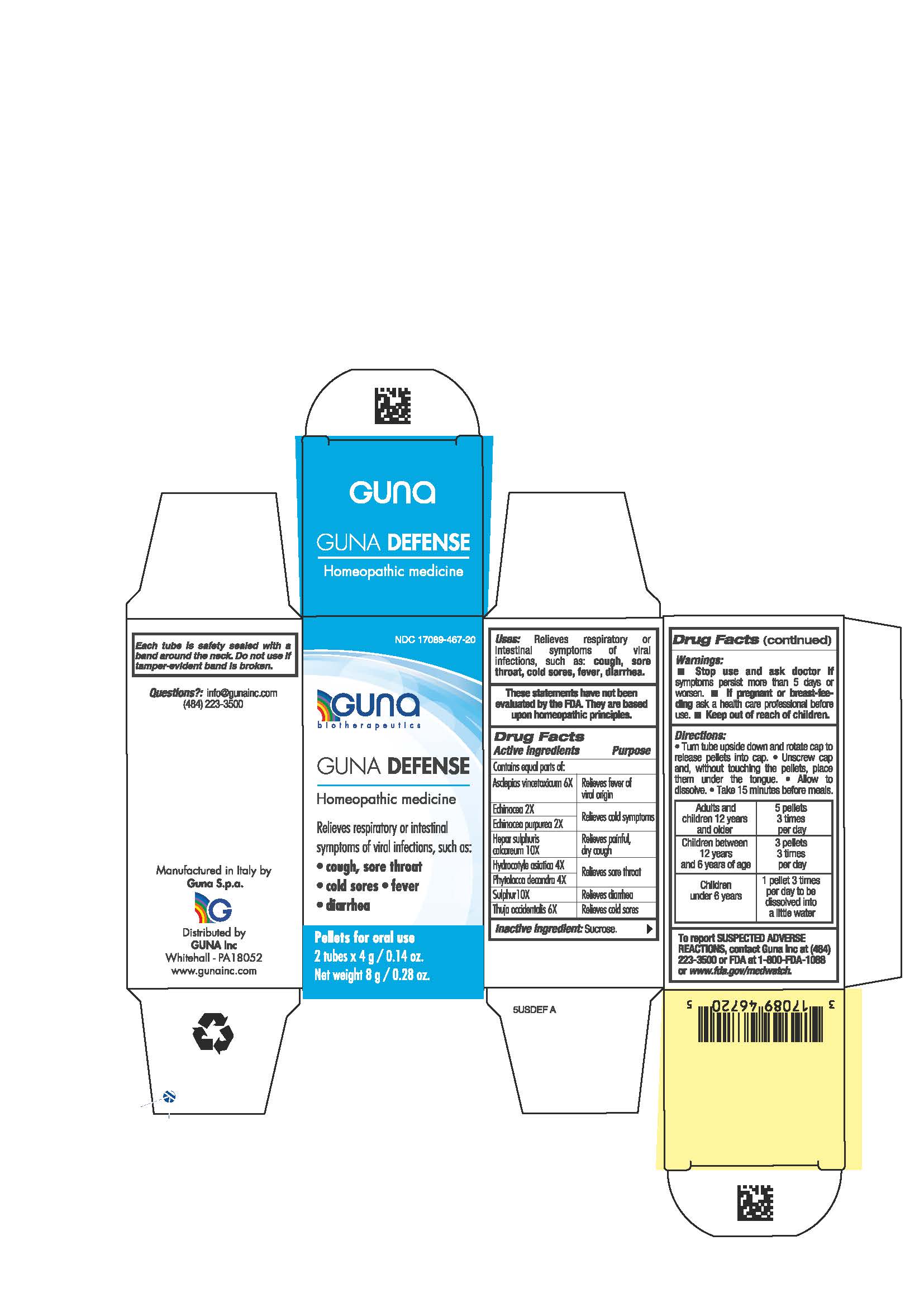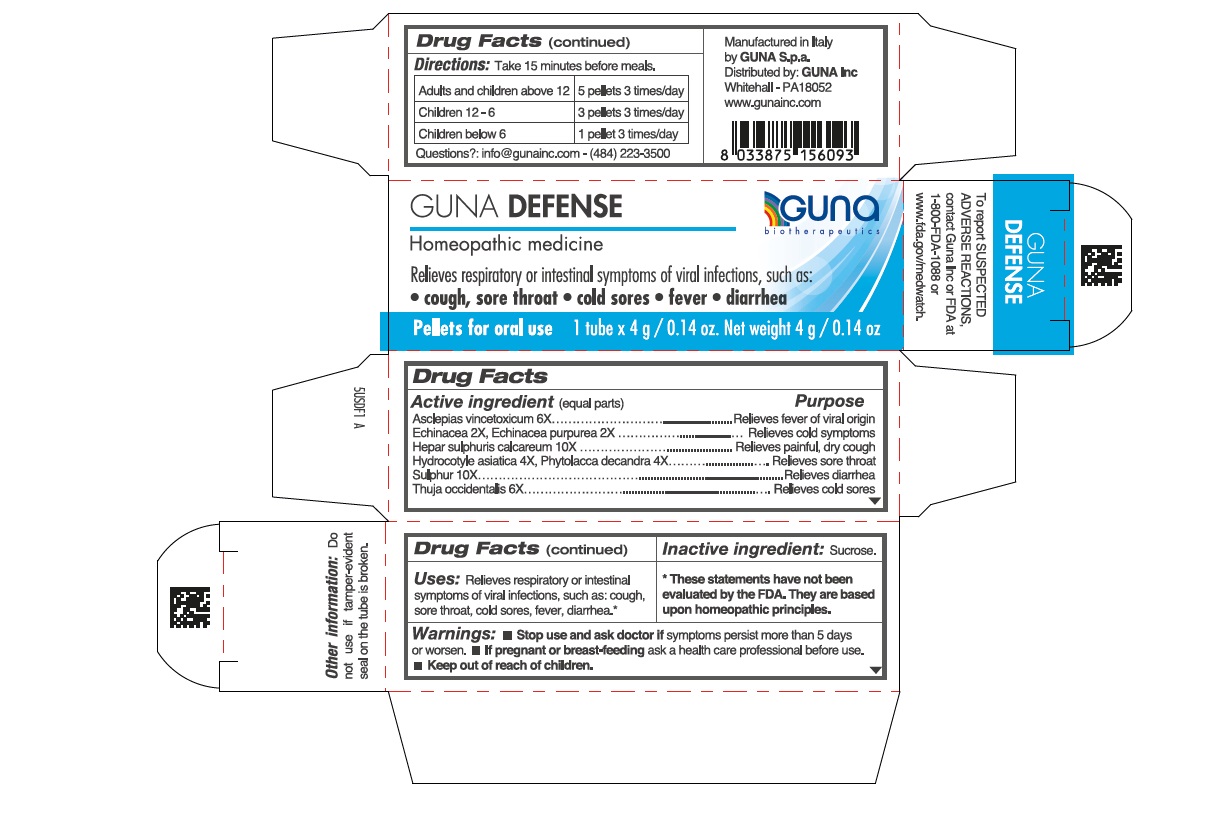 DRUG LABEL: GUNA DEFENSE
NDC: 17089-467 | Form: PELLET
Manufacturer: Guna spa
Category: homeopathic | Type: HUMAN OTC DRUG LABEL
Date: 20211215

ACTIVE INGREDIENTS: CENTELLA ASIATICA 4 [hp_X]/4 g; ECHINACEA ANGUSTIFOLIA WHOLE 2 [hp_X]/4 g; ECHINACEA PURPUREA 2 [hp_X]/4 g; CALCIUM SULFIDE 10 [hp_X]/4 g; THUJA OCCIDENTALIS LEAFY TWIG 6 [hp_X]/4 g; VINCETOXICUM HIRUNDINARIA ROOT 6 [hp_X]/4 g; PHYTOLACCA AMERICANA ROOT 4 [hp_X]/4 g; SULFUR 10 [hp_X]/4 g
INACTIVE INGREDIENTS: SUCROSE 4 g/4 g

GUNA DEFENSE

Uses:

Relieves respiratory or intestinal symptoms of viral infections, such as: cough, sore throat; cold sores; fever; diarrhea

Inactive ingredient: Sucrose.

DOSAGE AND ADMINISTRATION

- Adults and children 12 years and older 5 pellets 3 times per day
- Children between 12 years and 6 years of age 3 pellets 3 times per day
- Children under 6 years 1 pellet 3 times per day to be disoolved into a little water

QUESTIONS

info@gunainc.com
(484) 223-3500

DIRECTIONS

- Turn tube upside down and rotate cap to release pellets into cap.
- Unscrew cap and, without touching the pellets, place them under the tongue.
- Allow to dissolve.
- Take 15 minutes before meals.

WARNINGS

Keep out of reach of children

PREGNANCY

If pregnant or breast-feeding ask a health care professional before use.

WARNINGS

- Stop use and ask doctor if symptoms persist more than 5 days or worsen.
- If pregnant or breast-feeding ask a helath care professional before use
- keep out of reach of children

USES

Relieves respiratory or intestinal symptoms of viral infections, such as:

- cough, sore throat
- cold sores
- fever
- diarrhea

ACTIVE INGREDIENTS/PURPOSE

Asclepias vincetoxicum 6X Relieves fever of viral origin

Echinacea 2X Relieves cold symptoms

Echinacea purpurea 2X Relieves cold symptoms

Hepar sulphuris calc. 10X Relieves painful, dry cough

Hydrocotyle asiatica 4X Relieves sore throat

Phytolacca decandra 4X Relieves sore throat

Sulphur 10X Relieves diarrhea

Thuja occidentalis 6X Relieves cold sores

- Stop use and ask doctor if symptoms persist more than 5 days or worsen.
- If pregnant or breast-feeding ask a health professional before use.
- Keep out of reach of children.

- Keep out of reach of children